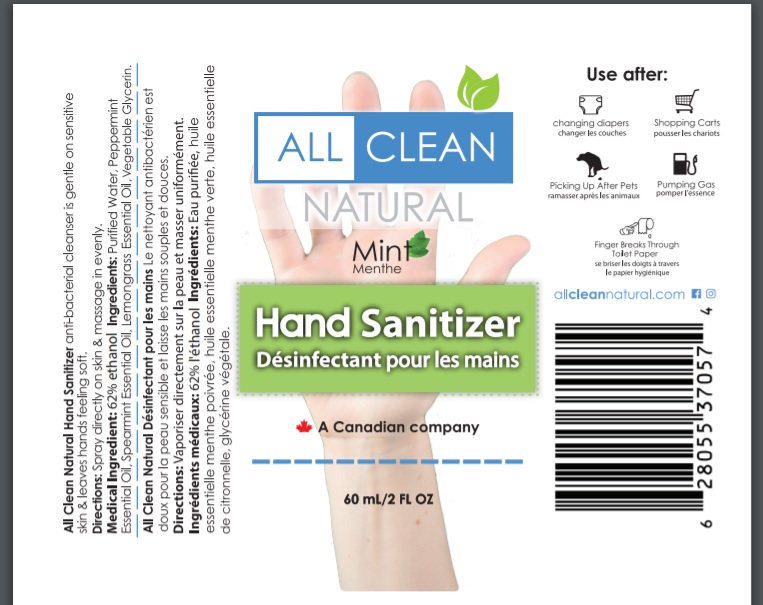 DRUG LABEL: Mint
NDC: 50157-301 | Form: SPRAY
Manufacturer: Brands International Corp
Category: otc | Type: HUMAN OTC DRUG LABEL
Date: 20200414

ACTIVE INGREDIENTS: ALCOHOL 620 mL/1000 mL
INACTIVE INGREDIENTS: GLYCERIN; PEPPERMINT OIL; SPEARMINT OIL; EAST INDIAN LEMONGRASS OIL; WATER

All Clean Natural Hand Sanitizer Spray

Active Ingredient - Ethanol 62%

Purpose - Antiseptic

Use

- to decrease bacteria on the skin and clean hands
- recommeded for repeated use

Warnings

for external use only

Flammable, keep away from fire or flame

KEEP OUT OF REACH OF CHILDREN

Keep out of children. If accidently swallowed, get medical helpor contact a Poison Control Center right away

USER SAFETY WARNINGS

Do not get into eyes, If contact occurs, rinse thoroughly with water

ASK DOCTOR/PHARMACIST

Discontinue Use if irritation or redness develops, If irritation persists for more than 72 hours, consult a doctor

Directions

- Spray directly to skin and massage evenly
- rub vigorously until dry
- supervise children in the use of this product

Other information

- may discolor certain fabrics or surfaces
- do not store above 110 F (43 C)

INACTIVE INGREDIENT

Purified water, Peppermint Essential Oil, Spearmint Essential Oil, Lemongrass Essential Oil, Vegetable Glycerin